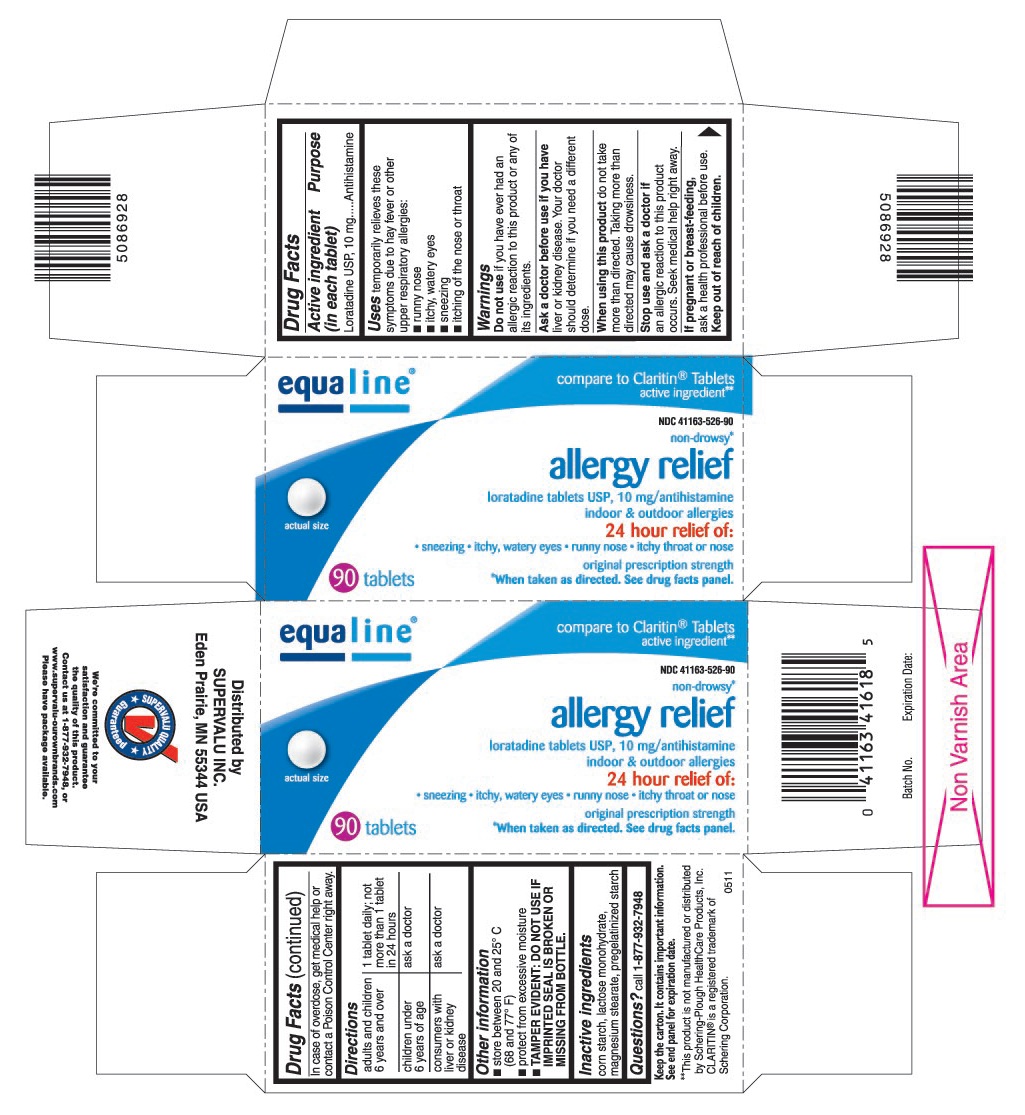 DRUG LABEL: Loratadine
NDC: 41163-526 | Form: TABLET
Manufacturer: SUPERVALU INC.
Category: otc | Type: HUMAN OTC DRUG LABEL
Date: 20120906

ACTIVE INGREDIENTS: LORATADINE 10 mg/1 1
INACTIVE INGREDIENTS: STARCH, CORN; STARCH, PREGELATINIZED CORN; LACTOSE MONOHYDRATE; MAGNESIUM STEARATE

Drug Facts

ACTIVE INGREDIENT (IN EACH TABLET)

Loratadine USP, 10 mg

PURPOSE

Antihistamine

USES

temporarily relieves these symptoms due to hay fever or other upper respiratory allergies:

- runny nose
- itchy, watery eyes
- sneezing
- itching of the nose or throat

WARNINGS

Do not use

if you have ever had an allergic reaction to this product or any of its ingredients.

Ask a doctor before use if you have

liver or kidney disease. Your doctor should determine if you need a different dose.

When using this product

do not take more than directed. Taking more than directed may cause drowsiness.

Stop use and ask a doctor if

an allergic reaction to this product occurs. Seek medical help right away.

If pregnant or breast-feeding,

ask a health professional before use.

Keep out of reach of children.

In case of overdose, get medical help or contact a Poison Control Center right away.

DIRECTIONS

adults and children 6 years and over | 1 tablet daily; not more than 1 tablet in 24 hours
children under 6 years of age | ask a doctor
consumers with liver or kidney disease | ask a doctor

OTHER INFORMATION

- store between 20 and 25° C (68 and 77° F)
- protect from excessive moisture
- TAMPER EVIDENT: DO NOT USE IF BLISTER UNITS ARE TORN, BROKEN OR SHOW ANY SIGNS OF TAMPERING.
- TAMPER EVIDENT: DO NOT USE IF IMPRINTED SEAL IS BROKEN OR MISSING FROM BOTTLE.

INACTIVE INGREDIENTS

corn starch, lactose monohydrate, magnesium stearate, pregelatinized starch

QUESTIONS?

call 1-800-406-7984

Keep the carton. It contains important information.

See end panel for expiration date.

Distributed by

SUPERVALU INC.

Eden Prairie, MN 55344 USA

1-877-932-7948

www.supervalu-ourownbrands.com

PRINCIPAL DISPLAY PANEL

equaline®

NDC 41163-526-90

non-drowsy*

allergy relief

loratadine tablets USP, 10 mg/antihistamine

indoor & outdoor allergies

24 hour relief of:

- sneezing
- itchy, watery eyes
- runny nose
- itchy throat or nose

original prescription strength

90 tablets

* When taken as directed. See drug facts panel.

compare to Claritin® Tablets active ingredient**

** This product is not manufactured or distributed by Schering-Plough HealthCare Products, Inc. CLARITIN® is a registered trademark of Schering Corporation.